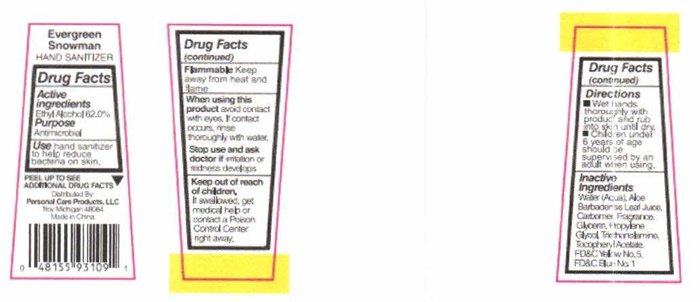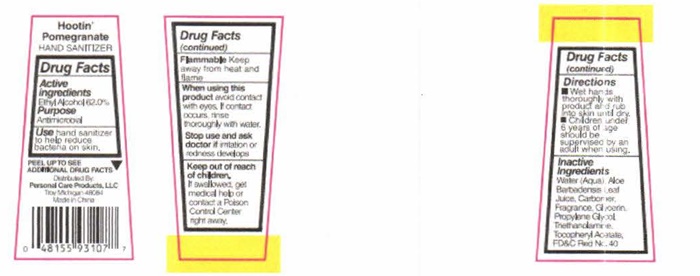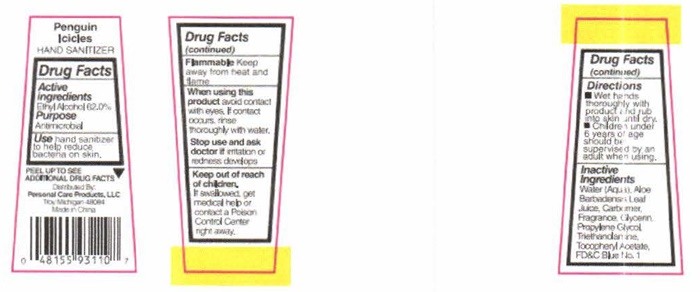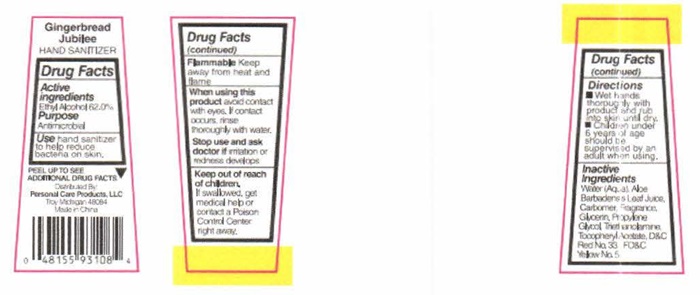 DRUG LABEL: Hootin Pomegranate
NDC: 29500-9317 | Form: LIQUID
Manufacturer: Personal Care Products LLC
Category: otc | Type: HUMAN OTC DRUG LABEL
Date: 20160918

ACTIVE INGREDIENTS: ALCOHOL 17.57 g/30 mL
INACTIVE INGREDIENTS: WATER; ALOE VERA LEAF; CARBOXYPOLYMETHYLENE; GLYCERIN; PROPYLENE GLYCOL; TROLAMINE; .ALPHA.-TOCOPHEROL ACETATE; FD&C RED NO. 40

Hootin' Pomegranate - 9317
Gingerbread Jubilee - 9318
Evergreen Snowman - 9399
Penguin Icicles - 9311

Drug Facts Active ingredients

Ethyl Alcohol 62.0%

Purpose

Antimicrobial

Keep out of reach of children. If swalowed, get medical help or contact a Poison Control Center right away.

Flammable

Keep away from heat and flame.

Use

hand sanitizer to help reduce bacteria on skin.

When using this product

avoid contact with eyes. If contact occurs, rinse thoroughly with water.

Stop use and ask a doctor if

irritation or redness develops.

Directions

- Wet hands thoroughly with product and rub into skin until dry.
- Children under 6 years of age should be supervised by an adult when using.

Inactive ingredients

Water (Aqua), Aloe Barbadensis Leaf Juice, Carbomer, Fragrance, Glycerin, Propylene Glycol, Triethanolamine, Tocopheryl Acetate. FD&C Blue No. 1, FD&C Red No. 40, FD&C Yellow No. 5, D&C Red No. 33

Hootin' Pomegranate, Gingerbread Jubilee, Evergreen Snowman, Penguin Icicles product label

Hootin' Pomegranate
HAND SANITIZER

PEEL UP TO SEE ADDITIONAL DRUG FACTS

Distributed By:
Personal Care Products, LLC
Troy Michigan 49064
Made in China

Gingerbread Jubilee
HAND SANITIZER

PEEL UP TO SEE ADDITIONAL DRUG FACTS

Distributed By:
Personal Care Products, LLC
Troy Michigan 49064
Made in China

Evergreen Snowman
HAND SANITIZER

PEEL UP TO SEE ADDITIONAL DRUG FACTS

Distributed By:
Personal Care Products, LLC
Troy Michigan 49064
Made in China

Penguin Icicles
HAND SANITIZER

PEEL UP TO SEE ADDITIONAL DRUG FACTS

Distributed By:
Personal Care Products, LLC
Troy Michigan 49064
Made in China